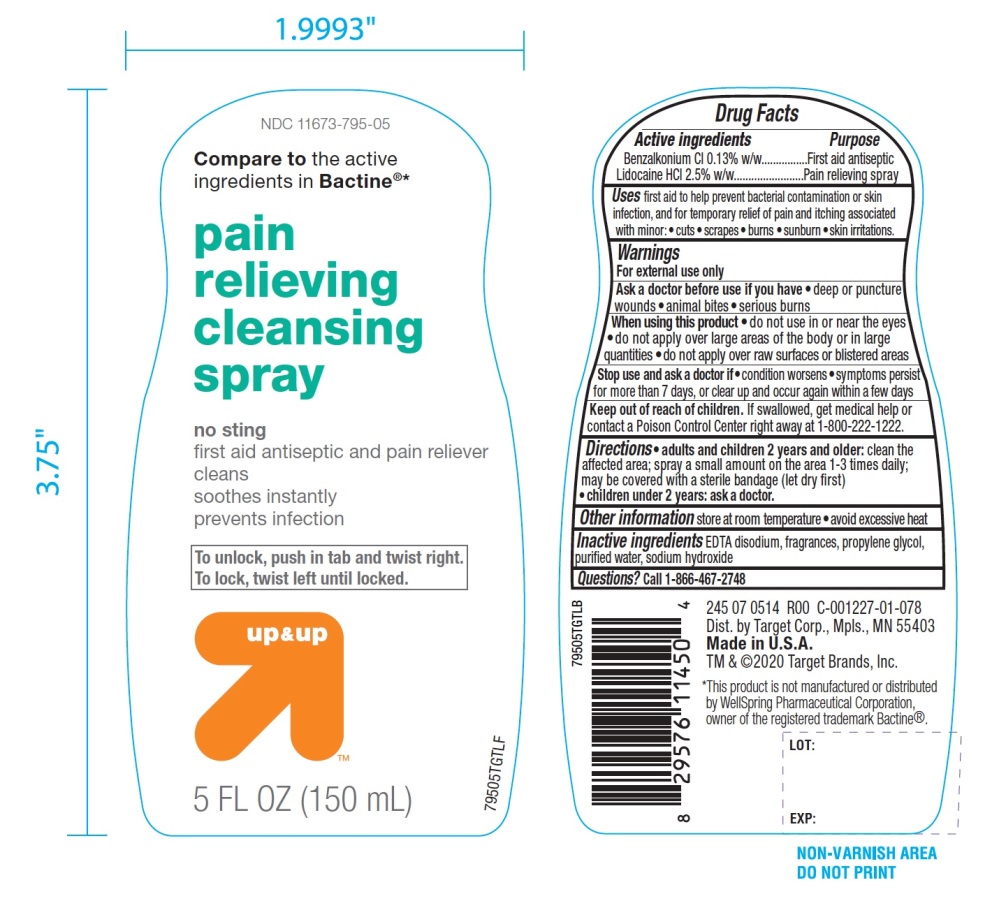 DRUG LABEL: Pain Relieving Cleansing
NDC: 11673-795 | Form: SPRAY
Manufacturer: TARGET CORPORATION
Category: otc | Type: HUMAN OTC DRUG LABEL
Date: 20251105

ACTIVE INGREDIENTS: BENZALKONIUM CHLORIDE 0.13 g/100 mL; LIDOCAINE HYDROCHLORIDE 2.5 g/100 mL
INACTIVE INGREDIENTS: EDETATE DISODIUM ANHYDROUS; PROPYLENE GLYCOL; WATER; SODIUM HYDROXIDE

Target Pain Relieving Cleansing Spray

Active ingredients

Benzalkonium Cl 0.13% w/w

Lidocaine HCI 2.5% w/w

Purpose

First aid antiseptic

Pain relieving spray

Uses

First aid to help prevent bacterial contamination or skin infection, and for temporary relief of pain and itching associated with minor:

- cuts
- scrapes
- burns
- sunburn
- skin irritations

Warnings

For external use only

Ask a doctor before use if you have

- deep or puncture wounds
- animal bites
- serious burns

When using this product

- do not use in or near the eyes
- do not apply over large area of the body or in large quantities
- do not apply over raw surfaces or blistered areas

Stop use and ask a doctor if

- condition worsens
- symptoms persist for more than 7 days, or clear up and occur again within a few days

Keep out of reach of children

If swallowed get medical help or contact a Poison Control Center right away at 1-800-222-1222

Directions

- adults and children 2 years and older:clean the affected area. spray small amount on the area 1-3 times daily; may be covered with sterile bandage (let dry first)
- children under 2 years:ask a doctor

Other information

- store at room temperature
- avoid excessive heat

Inactive ingredients

EDTA disodium, fragrance, propylene glycol, purified water, sodium hydroxide.

Principal Display Panel/Package Label

NDC# 11673-795-05

Compare to the active ingredients in Bactine®*

Pain Relieving

Cleansing Spray

NO STING

First Aid Antiseptic & Pain Reliever

- Cleans
- Soothes Instantly
- Prevents Infection

To unlock, push in tab and twist right. To lock, twist left until locked.

u p & up

5 FL OZ (150 mL)

DIST. by Target Corp.

Mpls., MN 55403

Made in U.S.A.

TM & ©2020 Target Brands, Inc.

*This product is not manufactured or distributed by Well Spring Pharmaceuticals Corporation, owner of the registered trademark Bactine®.